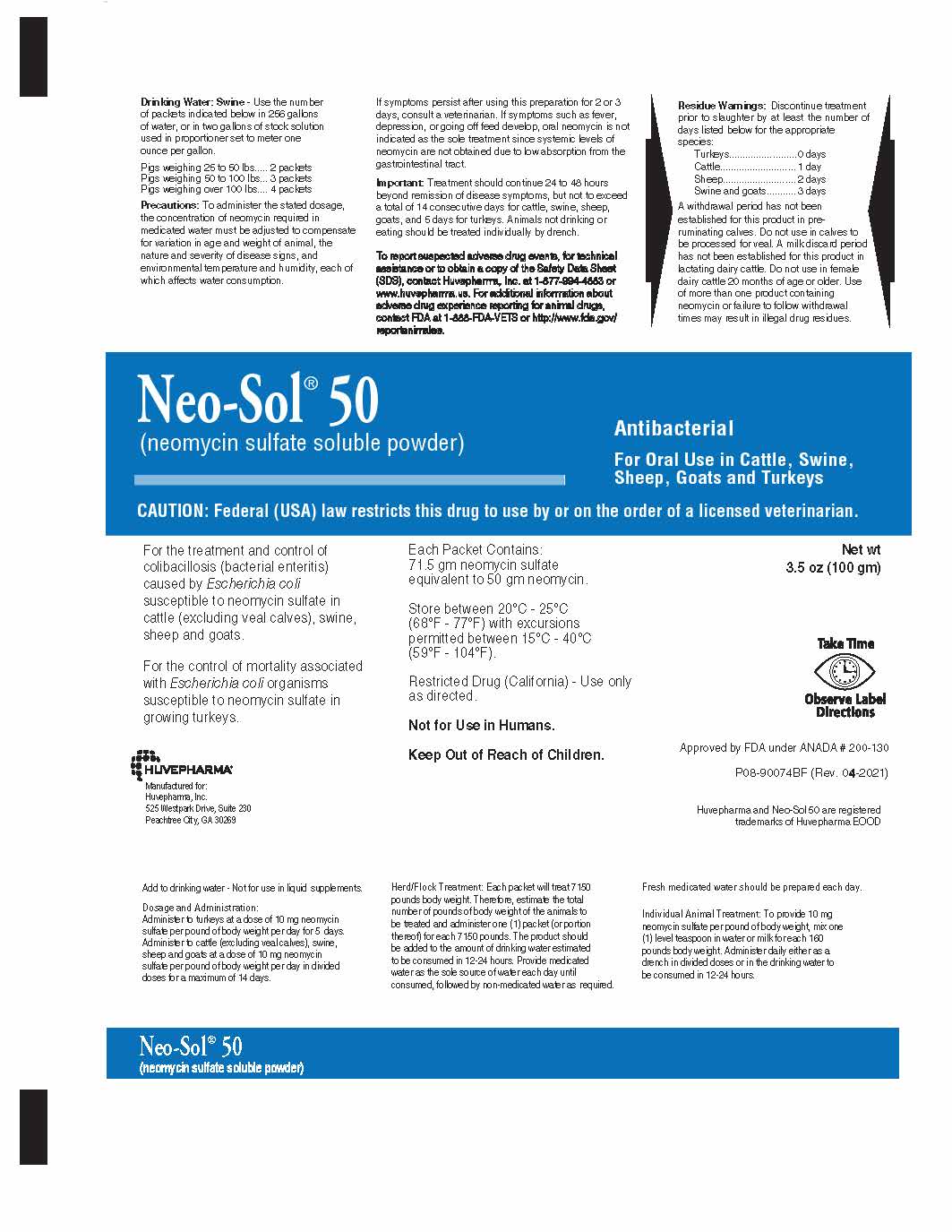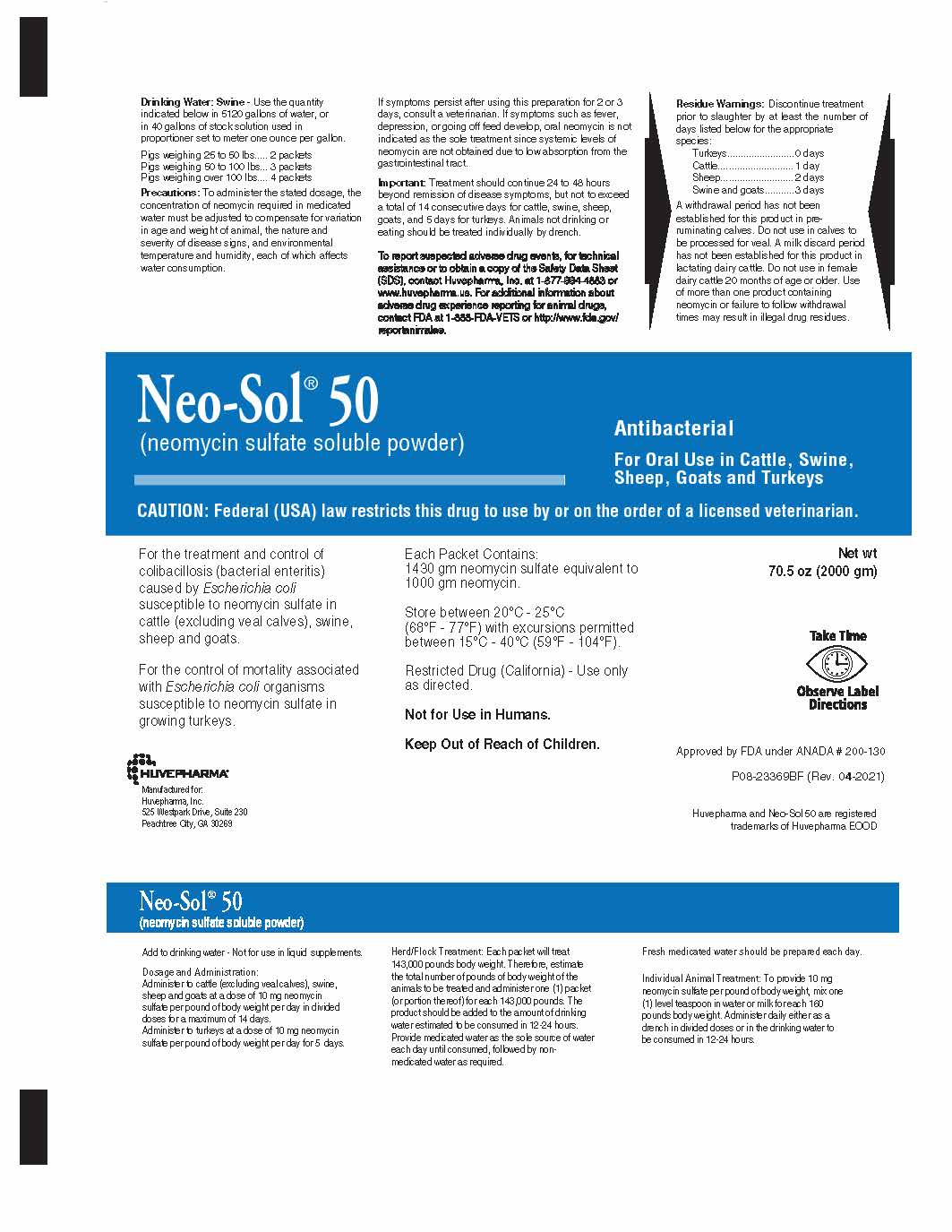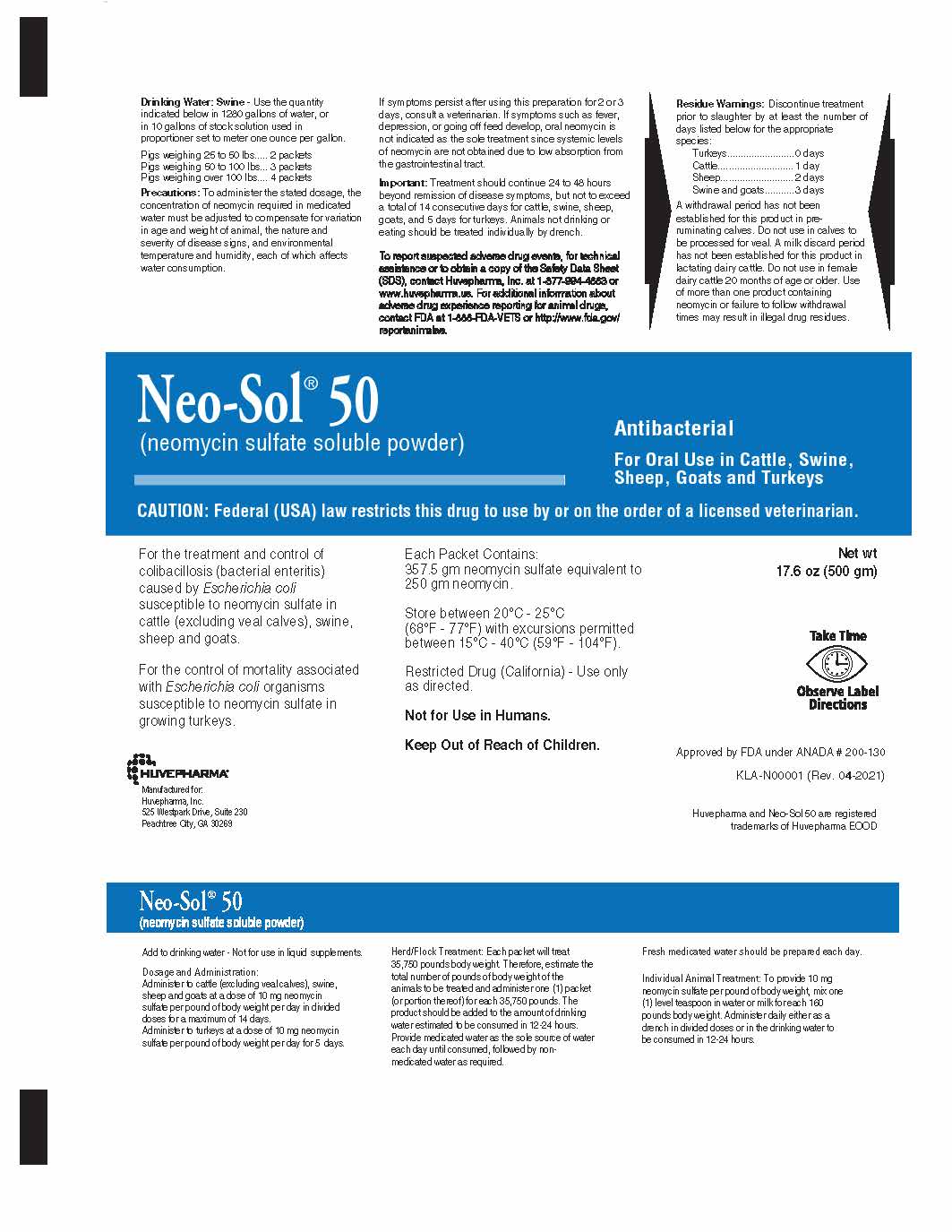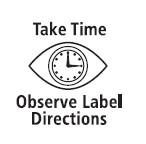 DRUG LABEL: Neo-Sol
NDC: 23243-6755 | Form: POWDER, FOR SOLUTION
Manufacturer: Huvepharma, Inc.
Category: animal | Type: PRESCRIPTION ANIMAL DRUG LABEL
Date: 20230630

ACTIVE INGREDIENTS: NEOMYCIN SULFATE 0.715 g/1 g

Neo-Sol® 50

100 Gram Packet Front Panel

Neo-Sol® 50
(neomycin sulfate soluble powder)

Antibacterial

For Oral Use in Cattle, Swine,
Sheep, Goats and Turkeys

GENERAL PRECAUTIONS

CAUTION: Federal (USA) law restricts this drug to use by or on the order of a licensed veterinarian.

INDICATIONS AND USAGE

For the treatment and control of colibacillosis (bacterial enteritis) caused
by Escherichia coli susceptible to neomycin sulfate in cattle (excluding
veal calves), swine, sheep and goats.

For the control of mortality associated with Escherichia coli organisms susceptible
to neomycin sulfate in growing turkeys.

Each Packet Contains:
71.5 gm neomycin sulfate
equivalent to 50 gm neomycin.

STORAGE AND HANDLING

Store between 20°C - 25°C

(68°F - 77°F) with excursions
permitted between 15°C - 40°C
(59°F - 104°F).

GENERAL PRECAUTIONS

Restricted Drug (California) - Use only as directed.

Not for Use in Humans.

Keep Out of Reach of Children

Net wt
3.5 oz (100 gm)

Approved by FDA under ANADA # 200-130

P08-90074BF (Rev 04-2021)

Huvepharma and Neo-Sol 50 are registered trademarks of Huvepharma EOOD

Huvepharma®
Manufactured for:
Huvepharma, Inc.
525 Westpark Dr., Suite 230
Peachtree City, GA 30269

DOSAGE AND ADMINISTRATION

Add to drinking water - Not for use in liquid supplements.

Dosage and Administration:
Administer to turkeys at a dose of 10 mg neomycin sulfate per pound of body weight per day for 5 days.
Administer to cattle (excluding veal calves), swine, sheep and goats at a dose of 10 mg neomycin sulfate
per pound of body weight per day in divided doses for a maximum of 14 days.

Herd/Flock Treatment:

Each packet will treat 7150 pounds body weight. Therefore, estimate the total number
of pounds of body weight of the animals to be treated and administer one (1) packet
(or portion thereof) for each 7150 pounds. The product should be added to the amount
of drinking water estimated to be consumed in 12-24 hours. Provide medicated water as
the sole source of water each day until consumed, followed by non-medicated water as
required.

Fresh medicated water should be prepared each day.

Individual Animal Treatment: To provide 10 mg neomycin sulfate per pound of body weight,
mix one (1) level teaspoon in water or milk for each 160 pounds body weight. Administer
daily either as a drench in divided doses or in the drinking water to be consumed in
12 - 24 hours.

Drinking Water: Swine - Use the number of packets indicated below in 256 gallons of water,
or in two gallons of stock solution used in proportioner set to meter one ounce per gallon.

Pigs weighing 25 to 50 lbs..... 2 packets
Pigs weighing 50 to 100 lbs... 3 packets
Pigs weighing over 100 lbs.... 4 packets

Precautions:

To administer the stated dosage, the concentration of neomycin required in medicated
water must be adjusted to compensate for variation in age and weight of animal, the
nature and severity of disease signs, and environmental temperature and humidity,
each of which affects water consumption.

If symptoms persist after using this preparation for 2 or 3 days, consult a veterinarian. If
symptoms such as fever, depression, or going off feed develop, oral neomycin is not indicated
as the sole treatment since systemic levels of neomycin are not obtained due to low absorption
from the gastrointestinal tract.

Important: Treatment should continue 24 to 48 hours beyond remission of disease symptoms,
but not to exceed a total of 14 consecutive days for cattle, swine, sheep, goats, and 5
days for turkeys. Animals not drinking or eating should be treated individually by drench.

ADVERSE REACTIONS

To report suspected adverse drug events, for technical assistance or to obtain a copy of the
Safety Data Sheet (SDS), contact Huvepharma, Inc. at 1-877-994-4883 or www.huvepharma.us. For
additional information about adverse drug experience reporting for animal drugs, contact FDA
at 1-888-FDA-VETS or http://www.fda.gov/reportanimalae.

RESIDUE WARNINGS:

Discontinue treatment prior to slaughter by at least the number of days listed below
for the appropriate species:

Turkeys ................... 0 days
Cattle ..................... 1 day
Sheep ..................... 2 days
Swine and goats ...... 3 days

A withdrawal period has not been established for this product in pre-ruminating calves.
Do not use in calves to be processed for veal. A milk discard period has not been
established for this product in lactating dairy cattle. Do not use in female dairy
cattle 20 months of age or older. Use of more than one product containing neomycin
or failure to follow withdrawal times may result in illegal drug residues.

2000 Gram Packet Front Panel

Neo-Sol® 50
(neomycin sulfate soluble powder)

Antibacterial

For Oral Use in Cattle, Swine,
Sheep, Goats and Turkeys

GENERAL PRECAUTIONS

CAUTION: Federal (USA) law restricts this drug to use by or on the order of a licensed veterinarian.

INDICATIONS AND USAGE

For the treatment and control of colibacillosis (bacterial enteritis) caused by Escherichia coli
susceptible to neomycin sulfate in cattle (excluding veal calves), swine, sheep and goats.

For the control of mortality associated with Escherichia coli organisms susceptible to
neomycin sulfate in growing turkeys.

Each Packet Contains:
1430 gm neomycin sulfate equivalent to 1000 gm neomycin.

STORAGE AND HANDLING

Store between 20°C - 25°C
(68°F - 77°F) with excursions
permitted between 15°C - 40°C
(59°F - 104°F).

GENERAL PRECAUTIONS

Restricted Drug (California) - Use only as directed.

Not for Use in Humans.

Keep Out of Reach of Children.

Net wt
70.5 oz (2000 gm)

Approved by FDA under ANADA # 200-130

P08-23369BF (04-2021)

Huvepharma and Neo-Sol 50 are registered trademarks of Huvepharma EOOD

Huvepharma
Manufactured for:
Huvepharma, Inc.
525 Westpark Dr., Suite 230
Peachtree City, GA 30269

DOSAGE AND ADMINISTRATION

Add to drinking water - Not for use in liquid supplements.

Dosage and Administration:
Administer to turkeys at a dose of 10 mg neomycin sulfate per pound of body weight per day for 5 days.
Administer to cattle (excluding veal calves), swine, sheep and goats at a dose of 10 mg neomycin sulfate
per pound of body weight per day in divided doses for a maximum of 14 days.

Herd/Flock Treatment:

Each packet will treat 143,000 pounds body weight. Therefore, estimate the total number
of pounds of body weight of the animals to be treated and administer one (1) packet
(or portion thereof) for each 143,000 pounds. The product should be added to the amount
of drinking water estimated to be consumed in 12-24 hours. Provide medicated water as
the sole source of water each day until consumed, followed by non-medicated water as
required.

Fresh medicated water should be prepared each day.

Individual Animal Treatment: To provide 10 mg neomycin sulfate per pound of body weight,
mix one (1) level teaspoon in water or milk for each 160 pounds body weight. Administer
daily either as a drench in divided doses or in the drinking water to be consumed in
12 - 24 hours.

Drinking Water: Swine - Use the quantity indicated below in 5120 gallons of water,
or in 40 gallons of stock solution used in proportioner set to meter one ounce per gallon.

Pigs weighing 25 to 50 lbs..... 2 packets
Pigs weighing 50 to 100 lbs... 3 packets
Pigs weighing over 100 lbs.... 4 packets

Precautions:

To administer the stated dosage, the concentration of neomycin required in medicated water
must be adjusted to compensate for variation in age and weight of animal, the nature and
severity of disease signs, and environmental temperature and humidity, each of which affects
water consumption.

If symptoms persist after using this preparation for 2 or 3 days, consult
a veterinarian. If symptoms such as fever, depression, or going off feed develop, oral
neomycin is not indicated as the sole treatment since systemic levels of neomycin are not
obtained due to low absorption from the gastrointestinal tract.

Important: Treatment should continue 24 to 48 hours beyond remission of disease symptoms,
but not to exceed a total of 14 consecutive days for cattle, swine, sheep, goats, and 5
days for turkeys. Animals not drinking or eating should be treated individually by drench.

ADVERSE REACTIONS

To report suspected adverse drug events, for technical assistance or to obtain a copy of the Safety Data Sheet
(SDS), contact Huvepharma, Inc. at 1-877-994-4883 or www.huvepharma.us. For additional information about
adverse drug experience reporting for animal drugs, contact FDA at 1-888-FDA-VETS or http://www.fda.gov/
reportanimalae.

RESIDUE WARNINGS:

Discontinue treatment prior to slaughter by at least the number of days listed below
for the appropriate species:

Turkeys ...................... 0 days
Cattle ........................ 1 day
Sheep ........................ 2 days
Swine and goats ......... 3 days

A withdrawal period has not been established for this product in pre-ruminating calves. Do not use in
calves to be processed for veal. A milk discard period has not been established for this product in
lactating dairy cattle. Do not use in female dairy cattle 20 months of age or older. Use of more than
one product containing neomycin or failure to follow withdrawal times may result in illegal drug residues.

500 Gram Packet Front Panel

Neo-Sol® 50
(neomycin sulfate soluble powder)

Antibacterial

For Oral Use in Cattle, Swine,
Sheep, Goats and Turkeys

GENERAL PRECAUTIONS

CAUTION: Federal (USA) law restricts this drug to use by or on the order of a licensed veterinarian.

INDICATIONS AND USAGE

For the treatment and control of colibacillosis (bacterial enteritis) caused by Escherichia coli
susceptible to neomycin sulfate in cattle (excluding veal calves), swine, sheep and goats.

For the control of mortality associated with Escherichia coli organisms susceptible to
neomycin sulfate in growing turkeys.

Each Packet Contains:
357.5 gm neomycin sulfate equivalent to 250 gm neomycin.

STORAGE AND HANDLING

Store between 20°C - 25°C
(68°F - 77°F) with excursions
permitted between 15°C - 40°C
(59°F - 104°F).

GENERAL PRECAUTIONS

Restricted Drug (California) - Use only as directed.

Not for Use in Humans.

Keep Out of Reach of Children.

Net wt
17.6 oz (500 g)

Approved by FDA under ANADA # 200-130

KLA-N00001 (Rev. 04-2021)

Huvepharma and Neo-Sol 50 are registered trademarks of Huvepharma EOOD

Huvepharma®
Manufactured for:
Huvepharma, Inc.
525 Westpark Dr., Suite 230
Peachtree City, GA 30269

DOSAGE AND ADMINISTRATION

Add to drinking water - Not for use in liquid supplements

Dosage and Administration:
Administer to cattle (excluding veal calves), swine, sheep and goats at a dose of 10 mg neomycin
sulfate per pound of body weight per day in divided doses for a maximum of 14 days.
Administer to turkeys at a dose of 10 mg neomycin sulfate per pound of body weight per day for 5 days.

Herd/Flock Treatment:

Each packet will treat 35,750 pounds body weight. Therefore, estimate the total number of
pounds of body weight of the animals to be treated and administer one (1) packet (or portion
thereof) for each 35,750 pounds. The product should be added to the amount of drinking water
estimated to be consumed in 12-24 hours. Provide medicated water as the sole source of water
each day until consumed, followed by non-medicated water as required.

Fresh medicated water should be prepared each day.

Individual Animal Treatment: To provide 10 mg neomycin sulfate per pound of body weight, mix one (1)
level teaspoon in water or milk for each 160 pounds body weight. Administer daily either as a drench
in divided doses or in the drinking water to be consumed in 12-24 hours.

Drinking Water: Swine - Use the quantity indicated below in 1280 gallons of water, or in 10
gallons of stock solution used in proportioner set to meter one ounce per gallon.

Pigs weighing 25 to 50 lbs ........... 2 packets
Pigs weighing 50 to 100 lbs ......... 3 packets
Pigs weighing over 100 lbs .......... 4 packets

PRECAUTIONS

Precautions: To administer the stated dosage, the concentration of neomycin required in medicated
water must be adjusted to compensate for variation in age and weight of animal, the nature and
severity of disease signs, and environmental temperature and humidity, each of which affects water
consumption.

If symptoms persist after using this preparation for 2 or 3 days, consult a veterinarian.
If symptoms such as fever, depression, or going off feed develop, oral neomycin is not indicated as the
sole treatment since systemic levels of neomycin are not obtained due to low absorption from the
gastrointestinal tract.

Important: Treatment should continue 24 to 48 hours beyond remission of disease symptoms, but not to exceed
a total of 14 consecutive days for cattle, swine, sheep, goats, and 5 days for turkeys. Animals not drinking
or eating should be treated individually by drench.

ADVERSE REACTIONS

To report suspected adverse drug events, for technical assistance or to obtain a copy of the Safety Data Sheet
(SDS), contact Huvepharma, Inc. at 1-877-994-4883 or www.huvepharma.us. For additional information about
adverse drug experience reporting for animal drugs, contact FDA at 1-888-FDA-VETS or http://www.fda.gov/
reportanimalae.

RESIDUE WARNINGS:

Discontinue treatment prior to slaughter by at least the number of days listed below for the
appropriate species:

Turkeys .................... 0 days
Cattle ...................... 1 day
Sheep ..................... 2 days
Swine and goats ...... 3 days

A withdrawal period has not been established for this product in pre-ruminating calves. Do not
use in calves to be processed for veal. A milk discard period has not been established for this
product in lactating dairy cattle. Do not use in female dairy cattle 20 months of age or older.
Use of more than one product containing neomycin or failure to follow withdrawal times may
result in illegal drug residues.